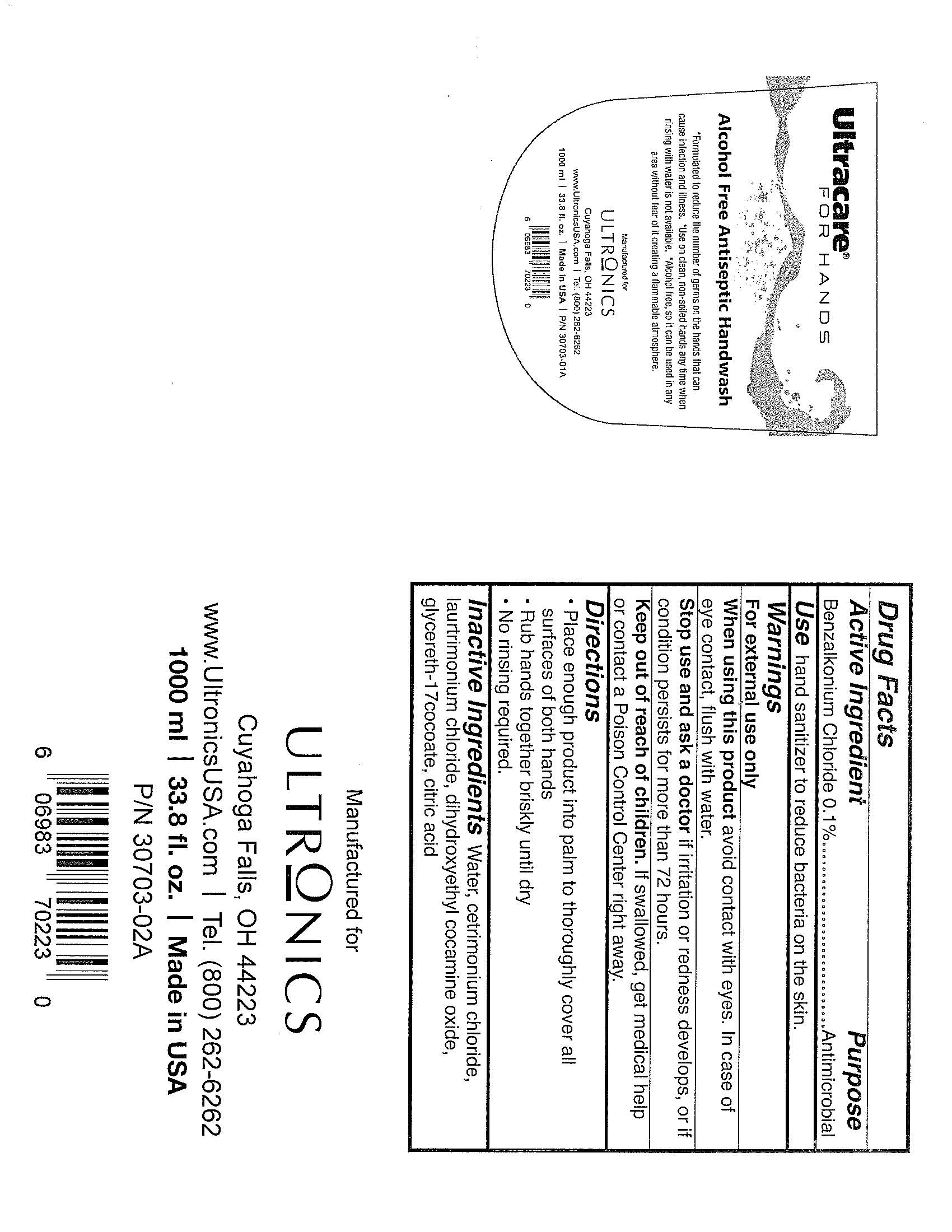 DRUG LABEL: Ultracare For Hands
NDC: 51614-0001 | Form: LIQUID
Manufacturer: Coltene Whaledent Inc
Category: otc | Type: HUMAN OTC DRUG LABEL
Date: 20120622

ACTIVE INGREDIENTS: BENZALKONIUM CHLORIDE 1 mg/1 mL
INACTIVE INGREDIENTS: WATER; CETRIMONIUM CHLORIDE; LAURTRIMONIUM CHLORIDE; DIHYDROXYETHYL COCAMINE OXIDE; CITRIC ACID MONOHYDRATE

Drug Facts

Active Ingredient

Benzalkonium Chloride 0.1%

Purpose

Antimicrobial

INDICATIONS AND USAGE

Use hand sanitizer to reduce bacteria on the skin.

Warnings

For external use only

When using this product avoid contact with eyes.

In case of eye contact, flush with water.

Stop use and ask a doctor if irritation or redness develops, or if condition persists for more than 72 hours.

Keep out of reach of children.

If swallowed, get medical help or contact a Poison Control Center right away.

Directions

Place enough product in palm to thoroughly cover all surfaces of both hands

Rub hands together briskly until dry

No rinsing required

Inactive Ingredients

Water, cetrimonium chloride, laurtrimonium chloride, dihydroxyethyl cocamine oxide, glycereth-17 cocoate, citric acid

PACKAGE LABEL

Ultracare

For Hands

Alcohol Free Antiseptic Handwash

Formulated to reduce the number of germs on the hands that can cause infection and illness.

Use on clean, non-soiled hands any time when rinsing with water is not available.

Alcohol free, so it can be used in any area without fear of it creating a flammable atmosphere.

Manufactured for

Ultronics

Cuyahoga Falls, OH 44223

www.UltronicsUSA.com Tel. (800) 262-6262

1000 ml 33.8 fl. oz. Made in USA P/N